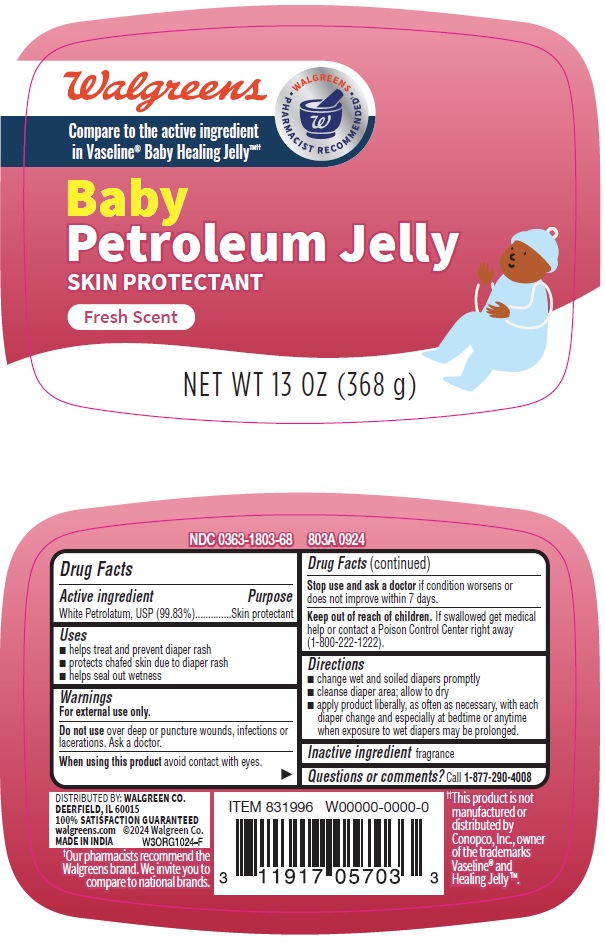 DRUG LABEL: Baby Petroleum Jelly
NDC: 0363-1803 | Form: JELLY
Manufacturer: WALGREENS
Category: otc | Type: HUMAN OTC DRUG LABEL
Date: 20241120

ACTIVE INGREDIENTS: WHITE PETROLATUM 99.83 g/100 g
INACTIVE INGREDIENTS: FRAGRANCE 13576

803A-Baby Petroleum Jelly_13 OZ

Active ingredient

White Petrolatum, USP (99.83%)

Purpose

Skin protectant

Uses

- helps treat and prevent diaper rash
- protects chafed skin due to diaper rash
- helps seal out wetness

WARNINGS

For external use only.

Do not use over deep or puncture wounds, infections or lacerations. Ask a doctor.

When using this product avoid contact with eyes.

Stop use and ask a doctor if condition worsens or does not improve within 7 days.

Keep out of reach of children. If swallowed get medical help or contact a Poison Control Center right away (1-800-222-1222).

Directions
• change wet and soiled diapers promptly
• cleanse diaper area; allow to dry
• apply product liberally, as often as necessary, with each diaper change and especially at bedtime or anytime when exposure to wet diapers may be prolonged.

INACTIVE INGREDIENT

fragrance

Questions or comments? Call 1-877-290-4008